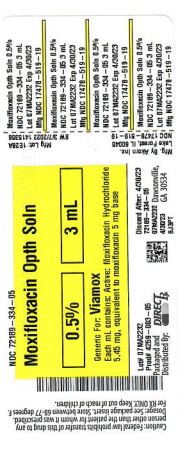 DRUG LABEL: MOXIFLOXACIN
NDC: 72189-334 | Form: SOLUTION/ DROPS
Manufacturer: Direct Rx
Category: prescription | Type: HUMAN PRESCRIPTION DRUG LABEL
Date: 20250121

ACTIVE INGREDIENTS: MOXIFLOXACIN HYDROCHLORIDE 5 mg/1 mL
INACTIVE INGREDIENTS: BORIC ACID; WATER; SODIUM HYDROXIDE; SODIUM CHLORIDE; HYDROCHLORIC ACID

MOXIFLOXACIN OPTH SOLN 0.5% 3ML

INDICATIONS AND USAGE

Moxifloxacin Ophthalmic Solution is indicated for the treatment of bacterial conjunctivitis caused by susceptible strains of the following organisms:

Corynebacterium species*

Micrococcus luteus*

Staphylococcus aureus

Staphylococcus epidermidis

Staphylococcus haemolyticus

Staphylococcus hominis

Staphylococcus warneri*

Streptococcus pneumoniae

Streptococcus viridans group

Acinetobacter lwoffii*

Haemophilus influenzae

Haemophilus parainfluenzae*

Chlamydia trachomatis

*Efficacy for this organism was studied in fewer than 10 infection

DOSAGE AND ADMINISTRATION

Instill one drop in the affected eye 3 times a day for 7 days. Moxifloxacin is for topical ophthalmic use.

DOSAGE FORMS AND STRENGTHS

Ophthalmic solution containing moxifloxacin 0.5%.

CONTRAINDICATIONS

Moxifloxacin ophthalmic solution is contraindicated in patients with a history of hypersensitivity to moxifloxacin, to other quinolones, or to any of the components in this medication.

WARNINGS AND PRECAUTIONS

5.1 Hypersensitivity Reactions

In patients receiving systemically administered quinolones, including moxifloxacin, serious and occasionally fatal hypersensitivity (anaphylactic) reactions have been reported, some following the first dose. Some reactions were accompanied by cardiovascular collapse, loss of consciousness, angioedema (including laryngeal, pharyngeal or facial edema), airway obstruction, dyspnea, urticaria, and itching. If an allergic reaction to moxifloxacin occurs, discontinue use of the drug. Serious acute hypersensitivity reactions may require immediate emergency treatment. Oxygen and airway management should be administered as clinically indicated.

5.2 Growth of Resistant Organisms with Prolonged Use

As with other anti-infectives, prolonged use may result in overgrowth of non-susceptible organisms, including fungi. If superinfection occurs, discontinue use and institute alternative therapy. Whenever clinical judgment dictates, the patient should be examined with the aid of magnification, such as slit-lamp biomicroscopy, and, where appropriate, fluorescein staining.

5.3 Avoidance of Contact Lens Wear

Patients should be advised not to wear contact lenses if they have signs or symptoms of bacterial conjunctivitis.

ADVERSE REACTIONS

Because clinical trials are conducted under widely varying conditions, adverse reaction rates observed in the clinical trials of a drug cannot be directly compared to the rates in the clinical trials of another drug and may not reflect the rates observed in practice.

The most frequently reported ocular adverse events were conjunctivitis, decreased visual acuity, dry eye, keratitis, ocular discomfort, ocular hyperemia, ocular pain, ocular pruritus, subconjunctival hemorrhage, and tearing. These events occurred in approximately 1% to 6% of patients.

Nonocular adverse events reported at a rate of 1% to 4% were fever, increased cough, infection, otitis media, pharyngitis, rash, and rhinitis.

DRUG INTERACTIONS

Drug-drug interaction studies have not been conducted with moxifloxacin ophthalmic solution. In vitro studies indicate that moxifloxacin does not inhibit CYP3A4, CYP2D6, CYP2C9, CYP2C19, or CYP1A2, indicating that moxifloxacin is unlikely to alter the pharmacokinetics of drugs metabolized by these cytochrome P450 isozymes.

USE IN SPECIFIC POPULATIONS

8.1 Pregnancy

Risk Summary

There are no adequate and well-controlled studies with moxifloxacin ophthalmic solution in pregnant women to inform any drug-associated risks.

Oral administration of moxifloxacin to pregnant rats and monkeys and intravenously to pregnant rabbits during the period of organogenesis did not produce adverse maternal or fetal effects at clinically relevant doses. Oral administration of moxifloxacin to pregnant rats during late gestation through lactation did not produce adverse maternal, fetal or neonatal effects at clinically relevant doses (see DATA).

Data

Animal Data

Embryo-fetal studies were conducted in pregnant rats administered with 20, 100, or 500 mg/kg/day moxifloxacin by oral gavage on Gestation Days 6 to 17, to target the period of organogenesis. Decreased fetal body weight and delayed skeletal development were observed at 500 mg/kg/day [277 times the human area under the curve (AUC) at the recommended human ophthalmic dose]. The No-Observed-Adverse-Effect-Level (NOAEL) for developmental toxicity was 100 mg/kg/day (30 times the human AUC at the recommended human ophthalmic dose).

Embryo-fetal studies were conducted in pregnant rabbits administered with 2, 6.5, or 20 mg/kg/day moxifloxacin by intravenous administration on Gestation Days 6 to 20, to target the period of organogenesis. Abortions, increased incidence of fetal malformations, delayed fetal skeletal ossification, and reduced placental and fetal body weights were observed at 20 mg/kg/day (1,086 times the human AUC at the recommended human ophthalmic dose), a dose that produced maternal body weight loss and death. The NOAEL for developmental toxicity was 6.5 mg/kg/day (246 times the human AUC at the recommended human ophthalmic dose).

Pregnant cynomolgus monkeys were administered moxifloxacin at doses of 10, 30, or 100 mg/kg/day by intragastric intubation between Gestation Days 20 and 50, targeting the period of organogenesis. At the maternal toxic doses of ≥30 mg/kg/day, increased abortion, vomiting, and diarrhea were observed. Smaller fetuses/reduced fetal body weights were observed at 100 mg/kg/day (2,864 times the human AUC at the recommended human ophthalmic dose). The NOAEL for fetal toxicity was 10 mg/kg/day (174 times the human AUC at the recommended human ophthalmic dose).

In a pre- and postnatal study, rats were administered moxifloxacin by oral gavage at doses of 20, 100, and 500 mg/kg/day from Gestation Day 6 until the end of lactation. Maternal death occurred during gestation at 500 mg/kg/day. Slight increases in the duration of pregnancy, reduced pup birth weight, and decreased prenatal and neonatal survival were observed at 500 mg/kg/day (estimated 277 times the human AUC at the recommended human ophthalmic dose). The NOAEL for pre- and postnatal development was 100 mg/kg/day (estimated 30 times the human AUC at the recommended human ophthalmic dose).

8.2 Lactation

Risk Summary

There is no data regarding the presence of moxifloxacin ophthalmic solution in human milk, the effects on the breastfed infants, or the effects on milk production/excretion to inform risk of moxifloxacin ophthalmic solution to an infant during lactation.

A study in lactating rats has shown transfer of moxifloxacin into milk following oral administration.

Systemic levels of moxifloxacin following topical ocular administration are low [see Clinical Pharmacology (12.3)], and it is not known whether measurable levels of moxifloxacin would be present in maternal milk following topical ocular administration.

The developmental and health benefits of breastfeeding should be considered along with the mother's clinical need for moxifloxacin ophthalmic solution and any potential adverse effects on the breastfed child from moxifloxacin ophthalmic solution.

8.4 Pediatric Use

The safety and effectiveness of moxifloxacin ophthalmic solution have been established in all ages. Use of moxifloxacin ophthalmic solution is supported by evidence from adequate and well controlled studies of moxifloxacin ophthalmic solution in adults, children, and neonates [see Clinical Studies (14)].

There is no evidence that the ophthalmic administration of moxifloxacin ophthalmic solution has any effect on weight bearing joints, even though oral administration of some quinolones has been shown to cause arthropathy in immature animals.

8.5 Geriatric Use

No overall differences in safety and effectiveness have been observed between elderly and younger patients.

DESCRIPTION

Moxifloxacin Ophthalmic Solution, USP 0.5% is a sterile solution for topical ophthalmic use. Moxifloxacin hydrochloride is an 8-methoxy fluoroquinolone anti-infective, with a diazabicyclononyl ring at the C7 position. The chemical name for moxifloxacin hydrochloride 1-Cyclopropyl-6-fluoro-1,4-dihydro-8-methoxy-7-[(4aS,7aS)-octahydro-6H-pyrrolol[3,4-b] pyridin-6-yl]-4-oxo-3-quinolinecarboxylic acid, monohydrochloride. The molecular formula for moxifloxacin hydrochloride is C12H24FN3O4•HCl and its molecular weight is 437.9 g/mol. The chemical structure is presented below:

[Chemical Structure]

Moxifloxacin hydrochloride is a slightly yellow to yellow crystalline powder.

Each mL of Moxifloxacin Ophthalmic Solution, USP contains 5.45 mg moxifloxacin hydrochloride, equivalent to 5 mg moxifloxacin base. Moxifloxacin Ophthalmic Solution contains Active: Moxifloxacin 0.5% (5 mg/mL); Inactives: Boric acid, sodium chloride, and water for injection. May also contain hydrochloric acid/sodium hydroxide to adjust pH to approximately 6.8.

Moxifloxacin Ophthalmic Solution, USP is an isotonic solution with an osmolality of approximately 290 mOsm/kg.

HOW SUPPLIED

Moxifloxacin Ophthalmic Solution, USP 0.5% is supplied as a sterile ophthalmic solution in a dispensing system consisting of a natural low density polyethylene bottle and dispensing plug and tan polypropylene closure. Tamper evidence is provided with a shrink band around the closure and neck area of the package.

NDC 17478-519-19 3 mL in 5 mL bottle

Storage: Store at 2° to 25°C (36° to 77°F).

PATIENT COUNSELING INFORMATION

Avoid Contamination of the Product

Advise patients not to touch the dropper tip to any surface to avoid contaminating the contents.

Avoid Contact Lens Wear

Advise patients not to wear contact lenses if they have signs and symptoms of bacterial conjunctivitis [see Warnings and Precautions (5.3)].

Hypersensitivity Reactions

Systemically administered quinolones including moxifloxacin have been associated with hypersensitivity reactions, even following a single dose. Instruct patients to discontinue use immediately and contact their physician at the first sign of a rash or allergic reaction [see Warnings and Precautions (5.1)].

AKRON
Manufactured by:
Akorn Operating Company LLC
Lake Forest, IL 60045

MX00N Rev. 11/21